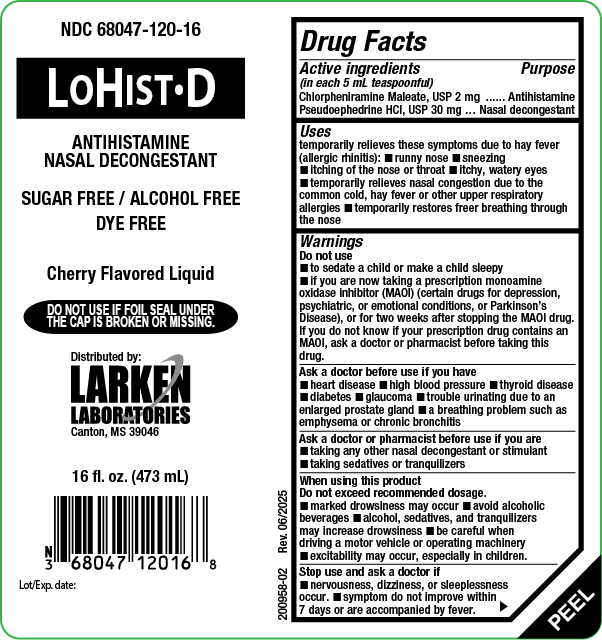 DRUG LABEL: LoHist


NDC: 68047-120 | Form: LIQUID
Manufacturer: Larken Laboratories, Inc.
Category: otc | Type: HUMAN OTC DRUG LABEL
Date: 20251015

ACTIVE INGREDIENTS: CHLORPHENIRAMINE MALEATE 2 mg/5 mL; PSEUDOEPHEDRINE HYDROCHLORIDE 30 mg/5 mL
INACTIVE INGREDIENTS: METHYLPARABEN; POLYETHYLENE GLYCOL 400; PROPYLPARABEN; WATER; SACCHARIN SODIUM ANHYDROUS; SORBITOL

LoHist D

Drug Facts

Active Ingredients

(In each 5 mL teaspoonful)

Chlorpheniramine Maleate, USP 2 mg

Pseudoephedrine HCl, USP 30 mg

Purpose

Chlorpheniramine Maleate Antihistamine

Pseudoephedrine HCl Nasal decongestant

Uses

temporarily relieves these symptoms due to hay fever (allergic rhinitis):

- runny nose
- sneezing
- itching of the nose or throat
- itchy, watery eyes
- temporarily relieves nasal congestion due to the common cold, hay fever or other upper respiratory allergies.
- temporarily restores freer breathing through the nose

Warnings

Do not use

- to sedate a child or make a child sleepy
- if you are now taking a prescription monoamine oxidase inhibitor (MAOI) (certain drugs for depression, psychiatric, or emotional conditions, or Parkinson's disease), or for 2 weeks after stopping the MAOI drug. If you do not know if your prescription drug contains an MAOI, ask a doctor or pharmacist before taking this drug.

Ask a Doctor before use if you have

- heart disease
- high blood pressure
- thyroid disease
- diabetes
- glaucoma

- trouble urinating due to an enlarged prostate gland
- a breathing problem such as emphysema or chronic bronchitis

Ask a doctor or pharmacist before use if you are.

- taking any other nasal decongestant or stimulant
- taking sedatives or tranquilizers

When using this product

Do not exceed recommended dosage.

- marked drowsiness may occur
- avoid alcoholic beverages
- alcohol, sedatives, and tranquilizers may increase drowsiness
- be careful when driving a motor vehicle or operating machinery
- excitability may occur, especially in children

Stop use and ask a doctor if

- nervousness, dizziness, or sleeplessness occur.
- symptoms do not improve within 7 days or are accompanied by fever.

If pregnant or breast feeding

ask a health professional before use.

Keep out of the reach of children

In case of overdose, get medical help or contact a Poison Control Center immediately.

Directions

Do not exceed 4 doses in a 24-hour period

Age | Dose
Adults and children over 12 years of age | 2 teaspoonfuls (10 mL) every 4 to 6 hours
Children 6 to under 12 years of age | 1 teaspoonful (5 mL) every 4 to 6 hours
Children under 6 years of age | Ask your doctor

Other information

- store at 20°-25°C (68°-77°F)
- very low sodium, contains less than 1 mg sodium per 5 mL teaspoonful

Inactive ingredients

cherry flavoring, methylparaben, polyethylene glycol, propylparaben, purified water saccharin sodium, and sorbitol

Questions or comments?

Call 1-601-855-7678 weekdays from 9:00 am to 4:00 pm CST or go to http://www.larkenlabs.com.

Package Label, Principal Display Panel

Figure 1:16 oz. bottle label